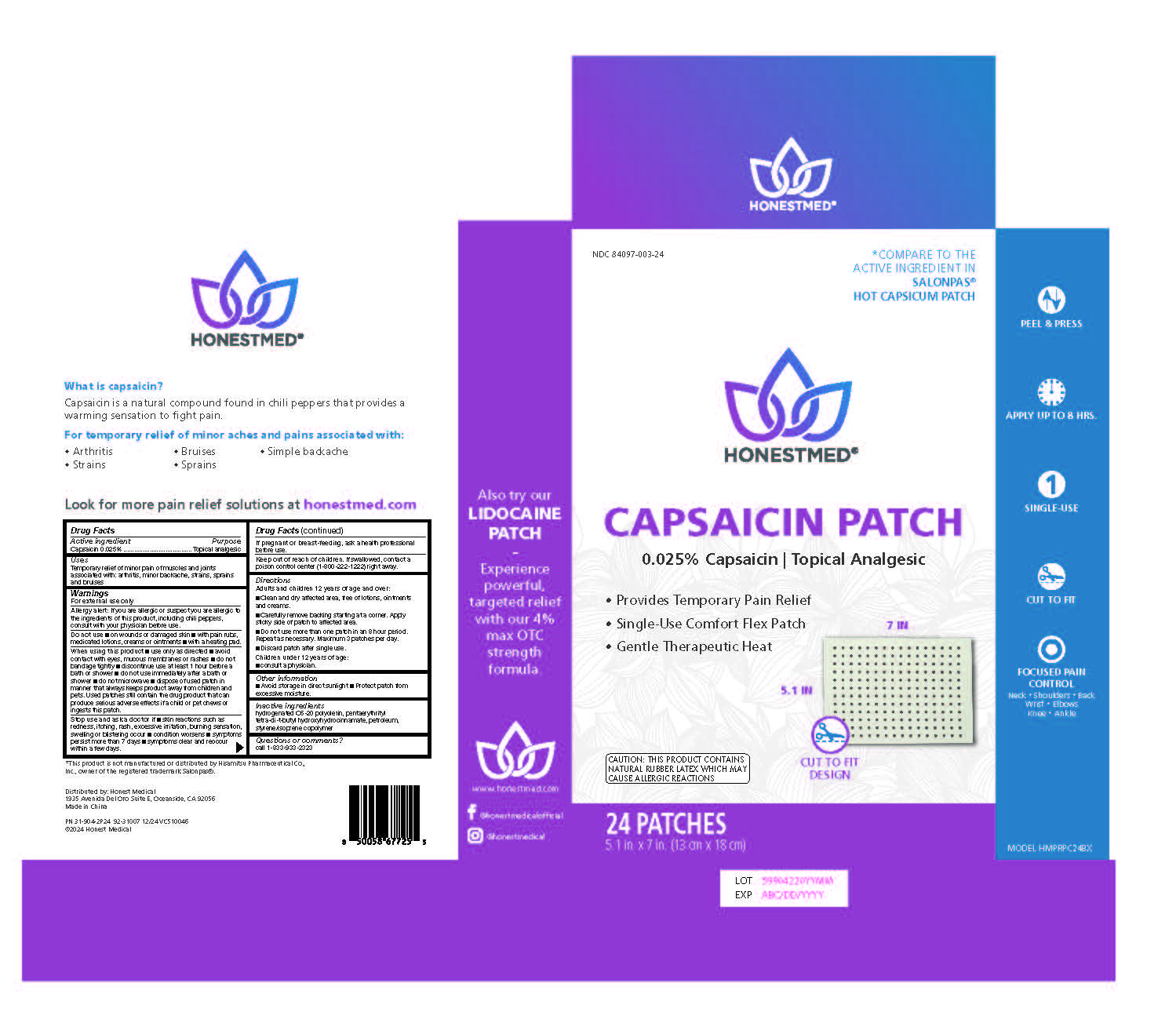 DRUG LABEL: Honest Med Capsaicin Patch
NDC: 84097-003 | Form: PATCH
Manufacturer: Proper Buys LLC
Category: otc | Type: HUMAN OTC DRUG LABEL
Date: 20251228

ACTIVE INGREDIENTS: CAPSAICIN 0.025 g/100 g
INACTIVE INGREDIENTS: HYDROGENATED POLYDECENE (550 MW); PENTAERYTHRITOL TETRAKIS(3-(3,5-DI-TERT-BUTYL-4-HYDROXYPHENYL)PROPIONATE); LIQUID PETROLEUM; STYRENE/ACRYLAMIDE COPOLYMER (MW 500000)

Honest Med Capsaicin Patch

Active Ingredients

Capsaicin: 0.025%...........................Topical Analgesic

Purpose

Topical Analgesic

Uses

Temporary relief of minor pain of muscles and joints associated with:

- Arthiritis
- Minor backache
- Strains
- Sprains
- Bruises

Warnings

For External use only

- Allergy alert: if you are allergic or suspect you are allergic to the ingredients listed below, including chili peppers, consult with your physician before use.

Do Not Use:

- On wounds or damaged skin
- with pain rubs, medicated lotions, creams or ointments
- with a heating pad.

When Using this product

■ use only as directed

■ avoid contact with eyes, mucous membranes or rashes

■ do not bandage tightly

■ discontinue use at least 1 hour before a bath or shower

■ do not use immediately after a bath or shower

■ do not microwave

■ dispose of used patch in manner that always keeps product away from children and pets. Used patches still contain the drug product that can produce serious adverse effects if a child or pet chews or ingests this patch.

Stop use and ask a doctor if

■ skin reactions such as redness, itching, rash, excessive irritation, burning sensation, swelling or blistering occur

■ condition worsens

■symptoms persist more than 7 days

■symptoms clear and reoccur within a few days.

If pregnant or breast-feeding

ask a health professional before use.

Keep Out of Reach of Children

if swallowed, contact a poison control center (1-800-222-1222) right away.

Directions for Use:

Adults and Childrens 12 Years of Age or Over

- Clean and dry affected area; free of lotions, ointments and creams
- Carefully remove backing starting at a corner. Apply sticky side of patch to affected area
- Do not use more than one patch in an 8-hour period. Repeat as necessary. Maximum 3 patches per day
- Discard after signle use

Children under 12 years of age:

- Consult a physician

Other Information

- avoid storage in direct sunlight
- Protect patch from excessive moisture

Inactive Ingredients:

Hydrogenated Poly, Pentaerythrityl Tetra-di-t-butyl Hydroxyhydrocinnamate, Petroleum, Styrene / Isoprene Copolymer

QUESTIONS

call 1-833-933-2323